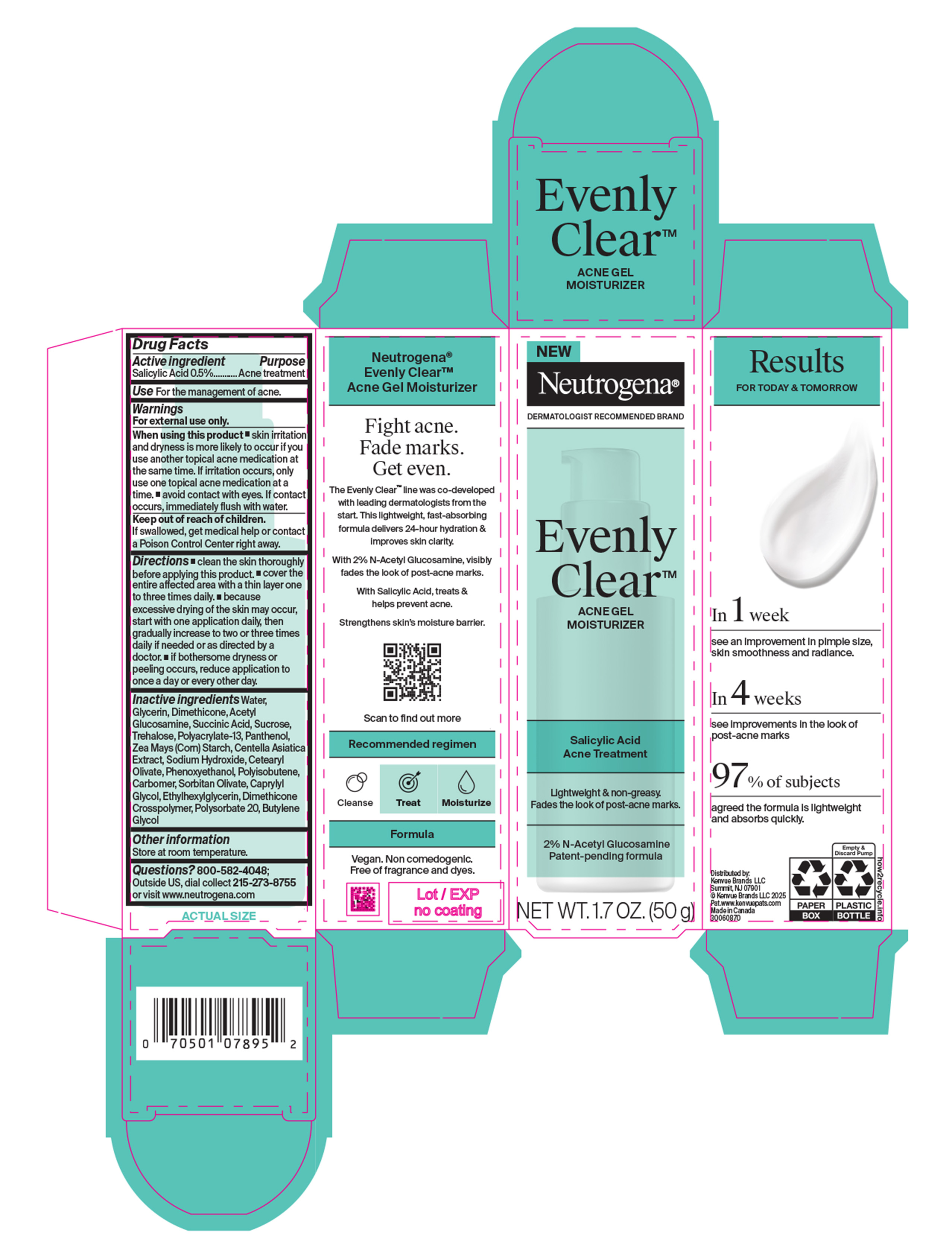 DRUG LABEL: Neutrogena Evenly Clear Acne Gel Moisturizer
NDC: 69968-0946 | Form: EMULSION
Manufacturer: Kenvue Brands LLC
Category: otc | Type: HUMAN OTC DRUG LABEL
Date: 20260302

ACTIVE INGREDIENTS: SALICYLIC ACID 5 mg/1 g
INACTIVE INGREDIENTS: PHENOXYETHANOL; ETHYLHEXYLGLYCERIN; PANTHENOL; CENTELLA ASIATICA TRITERPENOIDS; SODIUM HYDROXIDE; SUCCINIC ACID; TREHALOSE; ACETYL GLUCOSAMINE; CARBOMER; CETEARYL OLIVATE; CAPRYLYL GLYCOL; DIMETHICONE CROSSPOLYMER; POLYSORBATE 20; BUTYLENE GLYCOL; DIMETHICONE; SORBITAN OLIVATE; WATER; GLYCERIN; SUCROSE; POLYACRYLATE-13; ZEA MAYS (CORN) STARCH

Neutrogena Evenly Clear Acne Gel Moisturizer

Drug Facts

ACTIVE INGREDIENT

Salicylic Acid (0.5%)

PURPOSE

Acne treatment

Uses

For the management of acne.

Warnings

- For external use only

When using this product ▪ skin irritation and dryness is more likely to occur if you use another topical acne medication at the same time. If irritation occurs, only use one topical acne medication at a time. ▪ avoid contact with eyes. If contact occurs, immediately flush with water.

Keep out of reach of children. If swallowed, get medical help or contact a Poison Control Center right away.

Directions

- clean the skin thoroughly before applying this product. ▪ cover the entire affected area with a thin layer one to three times daily. ▪ because excessive drying of the skin may occur, start with one application daily, then gradually increase to two or three times daily if needed or as directed by a doctor. ▪ if bothersome dryness or peeling occurs, reduce application to once a day or every other day.

Inactive ingredients

Water, Glycerin, Dimethicone, Acetyl Glucosamine, Succinic Acid, Sucrose,Trehalose, Polyacrylate-13, Panthenol, Zea Mays (Corn) Starch, Centella Asiatica Extract, Sodium Hydroxide, Cetearyl Olivate, Phenoxyethanol, Polyisobutene, Carbomer, Sorbitan Olivate, Caprylyl Glycol, Ethylhexylglycerin, Dimethicone Crosspolymer, Polysorbate 20, Butylene Glycol

Other information

Store at room temperature.

Questions?

800-582-4048; Outside US, dial collect 215-273-8755 or visit www.neutrogena.com

Distributed by:

Kenvue Brands LLC
Summit, NJ 07901

PRINCIPAL DISPLAY PANEL - 50g Bottle in carton label

NEW

Neutrogena®

DERMATOLOGIST RECOMMENDED BRAND

Evenly

Clear™

ACNE GEL

MOISTURIZER

Salicylic Acid

Acne Treatment

Lightweight & non-greasy.

Fades the look of post-acne marks.

2% N-Acetyl Glucosamine

Patent- pending formula

NET WT. 1.7 OZ. (50 g)